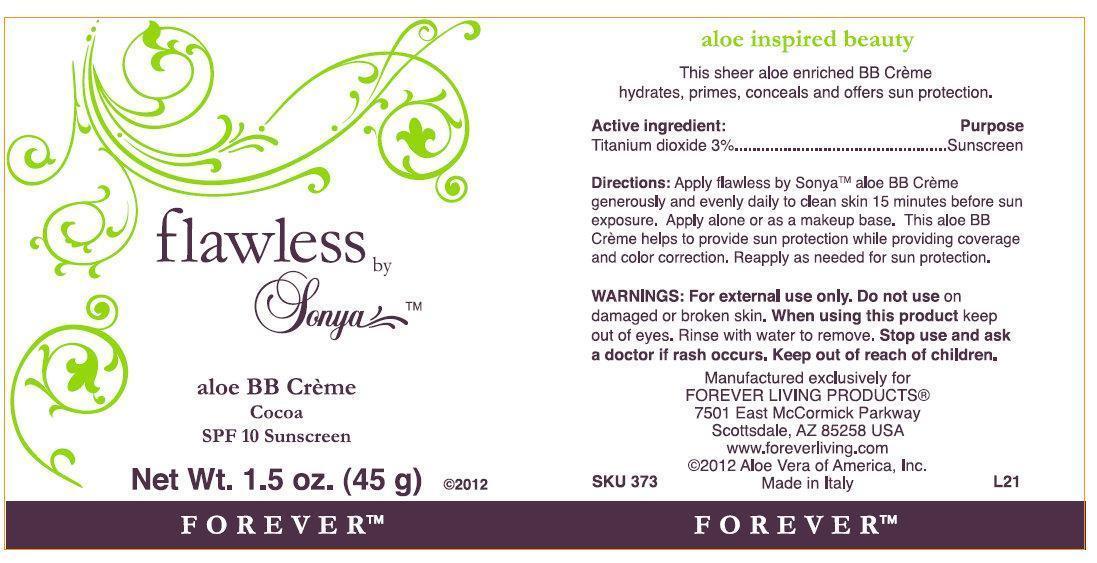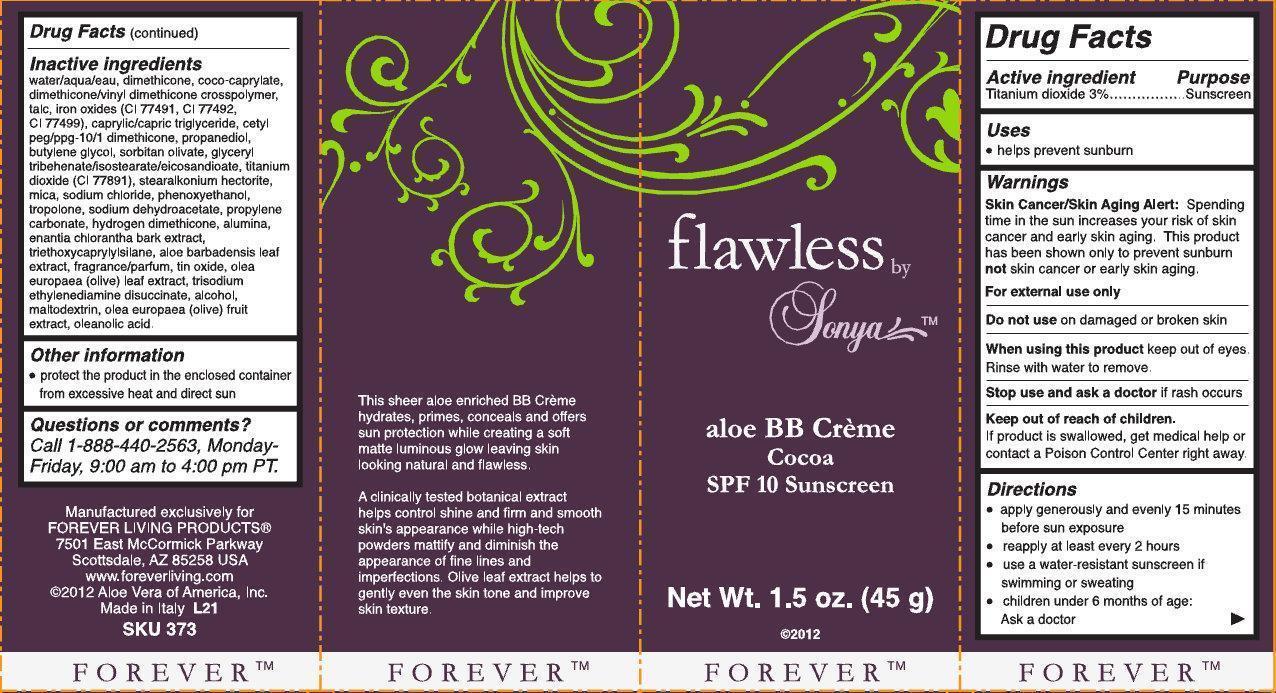 DRUG LABEL: flawless by Sonya aloe BB creme COCOA SPF 10 Sunscreen

NDC: 55891-002 | Form: CREAM
Manufacturer: Forever Living Products
Category: otc | Type: HUMAN OTC DRUG LABEL
Date: 20210422

ACTIVE INGREDIENTS: TITANIUM DIOXIDE 3 g/100 g
INACTIVE INGREDIENTS: WATER; DIMETHICONE; COCO-CAPRYLATE; DIMETHICONE/VINYL DIMETHICONE CROSSPOLYMER (SOFT PARTICLE); TALC; FERRIC OXIDE RED; FERRIC OXIDE YELLOW; FERROSOFERRIC OXIDE; MEDIUM-CHAIN TRIGLYCERIDES; CETYL PEG/PPG-10/1 DIMETHICONE (HLB 5); PROPANEDIOL; BUTYLENE GLYCOL; SORBITAN OLIVATE; TRIBEHENIN; MICA; SODIUM CHLORIDE; PHENOXYETHANOL; TROPOLONE; SODIUM DEHYDROACETATE; PROPYLENE CARBONATE; ALUMINUM OXIDE; ANNICKIA CHLORANTHA BARK; TRIETHOXYCAPRYLYLSILANE; ALOE VERA LEAF; STANNIC OXIDE; OLEA EUROPAEA LEAF; TRISODIUM ETHYLENEDIAMINE DISUCCINATE; ALCOHOL; MALTODEXTRIN; BLACK OLIVE; OLEANOLIC ACID

flawless by Sonya aloe BB creme COCOA SPF 10 Sunscreen

Active ingredient

Titanium dioxide 3%

Purpose

Sunscreen

Uses

- helps prevent sunburn

Warnings

Skin Cancer/Skin Aging Alert: Spending time in the sun increases your risk of skin cancer and early skin aging. This product has been shown only to prevent sunburn not skin cancer or early skin aging.
For external use only

Do not use

on damaged or broken skin

When using this product

keep out of eyes. Rinse with water to remove.

Stop use and ask a doctor

if rash occurs

Keep out of reach of children.

If products is swallowed, get medical help or contact a Poison Control Center right away.

Directions

- apply generously and evenly 15 minutes before sun exposure
- reapply at least every 2 hours
- use a water-resistant sunscreen if swimming or sweating
- children under 6 months of age: Ask a doctor

Inactive ingredients

water/aqua/eau, dimethicone, coco-caprylate, dimethicone/vinyl dimethicone crosspolymer, talc, iron oxides (CI 77491, CI 77492, CI 77499), caprylic/capric triglyceride, cetyl peg/ppg-10/1 dimethicone, propanediol, butylene glycol, sorbitan olivate, glyceryl tribehenate/isostearate/eicosandioate, titanium dioxide (CI 77891), stearalkonium hectorite, mica, sodium chloride, phenoxyethanol, tropolone, sodium dehydroacetate, propylene carbonate, hydrogen dimethicone, alumina, enantia chlorantha bark extract, triethoxycaprylylsilane, aloe barbadensis leaf extract, fragrance/parfum, tin oxide, olea europaea (olive) leaf extract, trisodium ethylenediamine disuccinate, alcohol, maltodextrin, olea europaea (olive) fruit extract, oleanolic acid.

Other information

- protect the product in the enclosed container from excessive heat and direct sun

Questions or comments?

Call 1-888-440-2563, Monday-Friday, 9:00 am to 4:00 pm PT.

FOREVER

This sheer aloe enriched BB Creme hydrates, primes, conceals and offers sun protection while creating a soft matte luminous glow leaving skin looking natural and flawless.
A clinically tested botanical extract helps control shine and firm and smooth skin's appearance while high-tech powders mattify and diminish the appearance of fine lines and imperfections. Olive leaf extract helps to gently even the skin tone and improve skin texture.
Manufactured exclusively for
FOREVER LIVING PRODUCTS
7501 East McCormick Parkway
Scottsdale, AZ 85258 USA
www.foreverliving.com
2012 Aloe Vera of America, Inc.
Made in Italy L21
SKU 373

PACKAGE LABEL

flawless by Sonya aloe BB creme Cocoa SPF 10 Sunscreen Net Wt. 1.5 oz. (45g) 2012